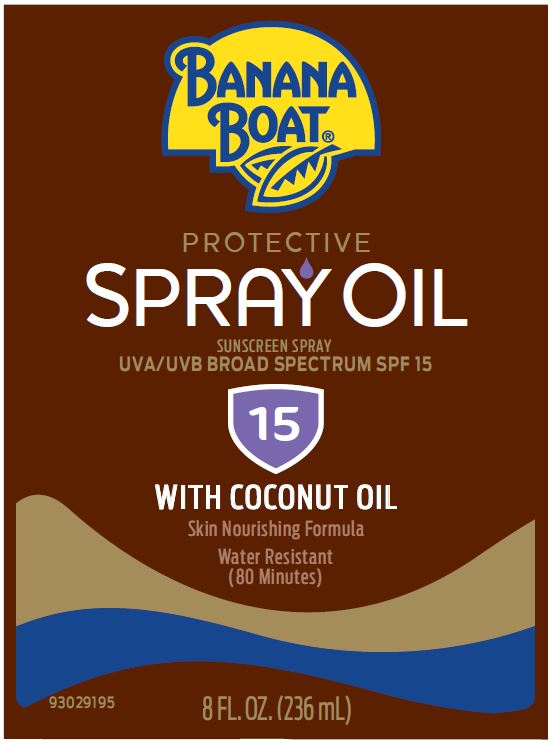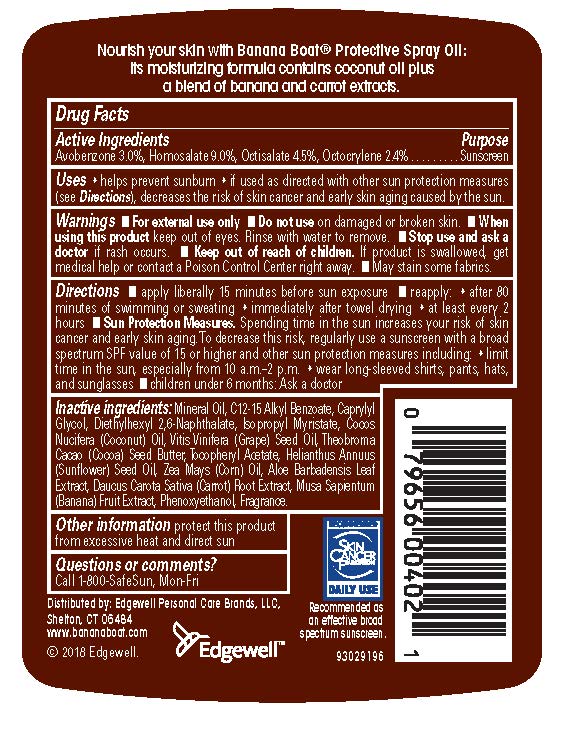 DRUG LABEL: Banana Boat
NDC: 63354-860 | Form: OIL
Manufacturer: Edgewell Personal Care Brands, LLC
Category: otc | Type: HUMAN OTC DRUG LABEL
Date: 20231128

ACTIVE INGREDIENTS: OCTISALATE 3.2 g/100 g; OCTOCRYLENE 2.4 g/100 g; HOMOSALATE 4.5 g/100 g; AVOBENZONE 3 g/100 g
INACTIVE INGREDIENTS: MINERAL OIL; CAPRYLYL GLYCOL; DIETHYLHEXYL 2,6-NAPHTHALATE; ISOPROPYL MYRISTATE; COCONUT OIL; GRAPE SEED OIL; THEOBROMA CACAO WHOLE; .ALPHA.-TOCOPHEROL ACETATE; ALOE VERA LEAF; SUNFLOWER OIL; CORN OIL; CARROT; BANANA; PHENOXYETHANOL

Active ingredients

Avobenzone 3.0%, Homosalate 9.0%, Octisalate 4.5%, Octocrylene 2.4%

Purpose

Sunscreen

Uses

Helps prevent sunburn

Warnings

For external use only

May stain some fabrics

Do not use

on damaged or broken skin

When using this product

Keep out of eyes. Rinse with water to remove

Stop use and ask a doctor

if rash occurs

Keep out of reach of children

If product is swallowed, get medical help or contact a Poison Control Center right away.

Directions

• apply liberally 15 minutes before sun exposure • reapply: • after 80 minutes of swimming or sweating • immediately after towel drying • at least every 2 hours • Sun Protection Measures. Spending time in the sun increases your risk of skin cancer and early skin aging. To decrease this risk, regularly use a sunscreen with a Broad Spectrum SPF value of 15 or higher and other sun protection measures including: • limit time in the sun, especially from 10 a.m. - 2 p.m. • wear long-sleeved shirts, pants, hats, and sunglasses • children under 6 months: Ask a doctor

Inactive ingredients

Mineral Oil, C12-15 Alkyl Benzoate, Caprylyl Glycol, Diethylhexyl 2,6-Naphthalate, Isopropyl Myristate, Coconut Oil, Grape Seed Oil, Theobroma Cacao (Cocoa) Seed Butter (Cocoa Butter),Tocopheryl Acetate, Helianthus Annuus (Sunflower) Seed Oil, Zea Mays (Corn) Oil, Aloe Barbadensis Leaf Extract, Daucus Carota Sativa (Carrot) Root Extract, Musa Sapientum (Banana) Fruit Extract,Phenoxyethanol, Fragrance.

Other Information

protect this product from excessive heat and direct sun

Questions & comments?

Call 1-800-SafeSun, mon-fri

PACKAGE LABEL

BANANA
BOAT®
PROTECTIVE
SPRAY OIL
SUNSCREEN SPRAY
UVA/UVB BROAD SPECTRUM SPF 15
15
WITH COCONUT OIL
Skin Nourishing Formula
Water Resistant
(80 Minutes)
8 FL. OZ. (236 mL)